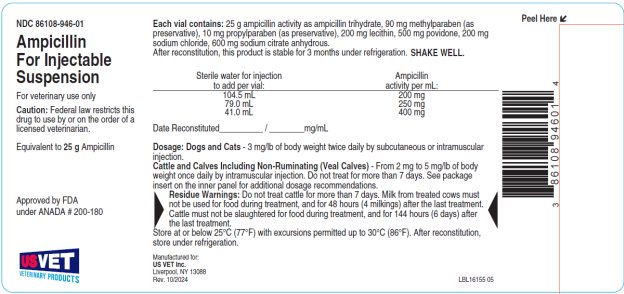 DRUG LABEL: Ampicillin
NDC: 86108-946 | Form: INJECTION, POWDER, FOR SUSPENSION
Manufacturer: US Vet Inc
Category: animal | Type: PRESCRIPTION ANIMAL DRUG LABEL
Date: 20250314

ACTIVE INGREDIENTS: AMPICILLIN TRIHYDRATE 25 g/1 1
INACTIVE INGREDIENTS: METHYLPARABEN; PROPYLPARABEN; POVIDONE, UNSPECIFIED; SODIUM CHLORIDE; ANHYDROUS TRISODIUM CITRATE; SOYBEAN LECITHIN

AMPICILLIN FOR INJECTABLE SUSPENSION, Veterinary

CAUTION:

Federal law restricts this drug to use by or on the order of a licensed veterinarian.

DESCRIPTION:

Ampicillin for injectable suspension is a broad-spectrum penicillin which has bactericidal activity against a wide range of common gram-positive and gram-negative bacteria.

Each 25 g vial contains: 25 g ampicillin activity as ampicillin trihydrate, 90 mg methylparaben (as preservative), 10 mg propylparaben (as preservative), 200 mg lecithin, 500 mg povidone, 200 mg sodium chloride, 600 mg sodium citrate anhydrous.

INDICATIONS:

Ampicillin for injectable suspension has proved effective in the treatment of many infections previously beyond the spectrum of penicillin therapy. This drug is particularly indicated in the treatment of the following infections caused by susceptible strains of organisms:

Dogs and Cats - Respiratory Tract Infections: Upper respiratory infections, tonsillitis and bronchopneumonia due to hemolytic streptococci, Staphylococcus aureus, Escherichia coli, Proteus mirabilis and Pasteurella spp.

Urinary Tract Infections due to Proteus mirabilis, Escherichia coli, Staphylococcus spp., hemolytic streptococci and Enterococcus spp.

Gastrointestinal Infections due to Enterococcus spp., Staphylococcus spp. and Escherichia coli.

Skin, Soft Tissue and Post-Surgical Infections: Abscesses, pustular dermatitis, cellulitis and infections of the anal gland, due to Escherichia coli, Proteus mirabilis, hemolytic streptococci, Staphylococcus spp. and Pasteurella spp.

Cattle and Calves Including Non-Ruminating (Veal Calves) - Respiratory Tract Infections: Bacterial pneumonia (shipping fever, calf pneumonia and bovine pneumonia) caused by Aerobacter spp., Klebsiella spp., Staphylococcus spp., Streptococcus spp., Pasteurella multocida and E. coli susceptible to ampicillin trihydrate.

DOSAGE:

The dosage of ampicillin for injectable suspension will vary according to the animal being treated, the severity of the infection and the animal’s response.

Dogs and Cats - The recommended dose for dogs or cats is 3 mg/lb of body weight administered twice daily by subcutaneous or intramuscular injection.

Cattle and Calves Including Non-Ruminating (Veal Calves) - From 2 mg to 5 mg/lb of body weight once daily by intramuscular injection. Do not treat for more than 7 days.

In all species, 3 days treatment is usually adequate, but treatment should be continued for 48 to 72 hours after the animal has become afebrile or asymptomatic.

DIRECTIONS FOR USE:

The multi-dose dry-filled vials should be reconstituted to the desired concentration by adding the required amount of Sterile Water for Injection, USP, according to label directions. SHAKE WELL.

After reconstitution this product is stable for 3 months under refrigeration and will be white to pale yellow in color.

At the time of reconstitution the vial should be dated and the concentration noted on the label.

CONTRAINDICATIONS:

A history of allergic reactions to penicillin, cephalosporins or their analogues should be considered a contraindication for the use of this agent.

RESIDUE WARNINGS

DO NOT TREAT CATTLE FOR MORE THAN 7 DAYS.

MILK FROM TREATED COWS MUST NOT BE USED FOR FOOD DURING TREATMENT, AND FOR 48 HOURS (4 MILKINGS) AFTER THE LAST TREATMENT.

CATTLE MUST NOT BE SLAUGHTERED FOR FOOD DURING TREATMENT, AND FOR 144 HOURS (6 DAYS) AFTER THE LAST TREATMENT.

PRECAUTIONS:

Because it is a derivative of 6-aminopenicillanic acid, ampicillin for injectable suspension has the potential for producing allergic reactions. If they should occur, ampicillin for injectable suspension should be discontinued and the subject treated with the usual agents (antihistamines, pressor amines, corticosteroids).

CLINICAL PHARMACOLOGY:

The antimicrobial action of ampicillin is bactericidal, and only a small percentage of the antibiotic is serum-bound. Peak serum levels in dogs and cats are reached approximately one-half hour following subcutaneous or intramuscular injection, and in cattle 1 hour to 2 hours following intramuscular injection.

In vitro studies have demonstrated sensitivity of the following organisms to ampicillin: gram-positive bacteria - alpha- and beta-hemolytic streptococci, staphylococci (non-penicillinase-producing), Bacillus anthracis and most strains of enterococci and clostridia; gram-negative bacteria - Proteus mirabilis, E. coli and many strains of Salmonella and Pasteurella multocida.

The drug does not resist destruction by penicillinase and, hence, is not effective against strains of staphylococci resistant to penicillin G. Susceptibility tests should be conducted to estimate the in vitro susceptibility of bacterial isolates to ampicillin.

STORAGE:

Store at or below 25ºC (77ºF) with excursions permitted up to 30ºC (86ºF). After reconstitution, store under refrigeration.

HOW SUPPLIED:

Ampicillin for injectable suspension is supplied in vials containing 25 grams ampicillin activity as ampicillin trihydrate.

NDC 86108-946-01 25 g per vial

Manufactured for:

US Vet Inc. Liverpool, NY 13088

Rev. 10/2024

LBL16155 05

PACKAGE/LABEL PRINCIPAL DISPLAY PANEL

NDC 86108-946-01 Ampicillin for Injectable Suspension For Veterinary Use only Caution: Federal Law restricts this drug to use by or on the order of a licensed veterinarian. Equivalent to 25 g Ampicillin. Approved by FDA under ANADA # 200-180

Each vial contains: 25 g ampicillin activity as ampicillin trihydrate, 90 mg methylparaben (as preservative), 10 mg propylparaben (as preservative), 200 mg lecithin, 500 mg povidone, 200 mg sodium chloride, 600 mg sodium citrate anhydrous.

After reconstitution, this product is stable for 3 months under refrigeration. SHAKE WELL. Date Reconstituted__________ / ________mg/mL READ INNER PANEL. Dosage: Dogs and Cats - 3 mg/lb of body weight twice daily by subcutaneous or intramuscular injection. Cattle and Calves Including Non-Ruminating (Veal Calves) - From 2 mg to 5 mg/lb of body weight once daily by intramuscular injection. Do not treat for more than 7 days. See inner panel for additional dosage recommendations. Residue Warnings: Do not treat cattle for more than 7 days. Milk from treated cows must not be used for food during treatment, and for 48 hours (4 milkings) after the last treatment. Cattle must not be slaughtered for food during treatment, and for 144 hours (6 days) after the last treatment. Store at or below 25ºC (77ºF) with excursions permitted up to 30ºC (86ºF). After reconstitution, store under refrigeration.

Manufactured for:

US Vet Inc. Liverpool, NY 13088 Rev. 10/2024 LBL16155 05